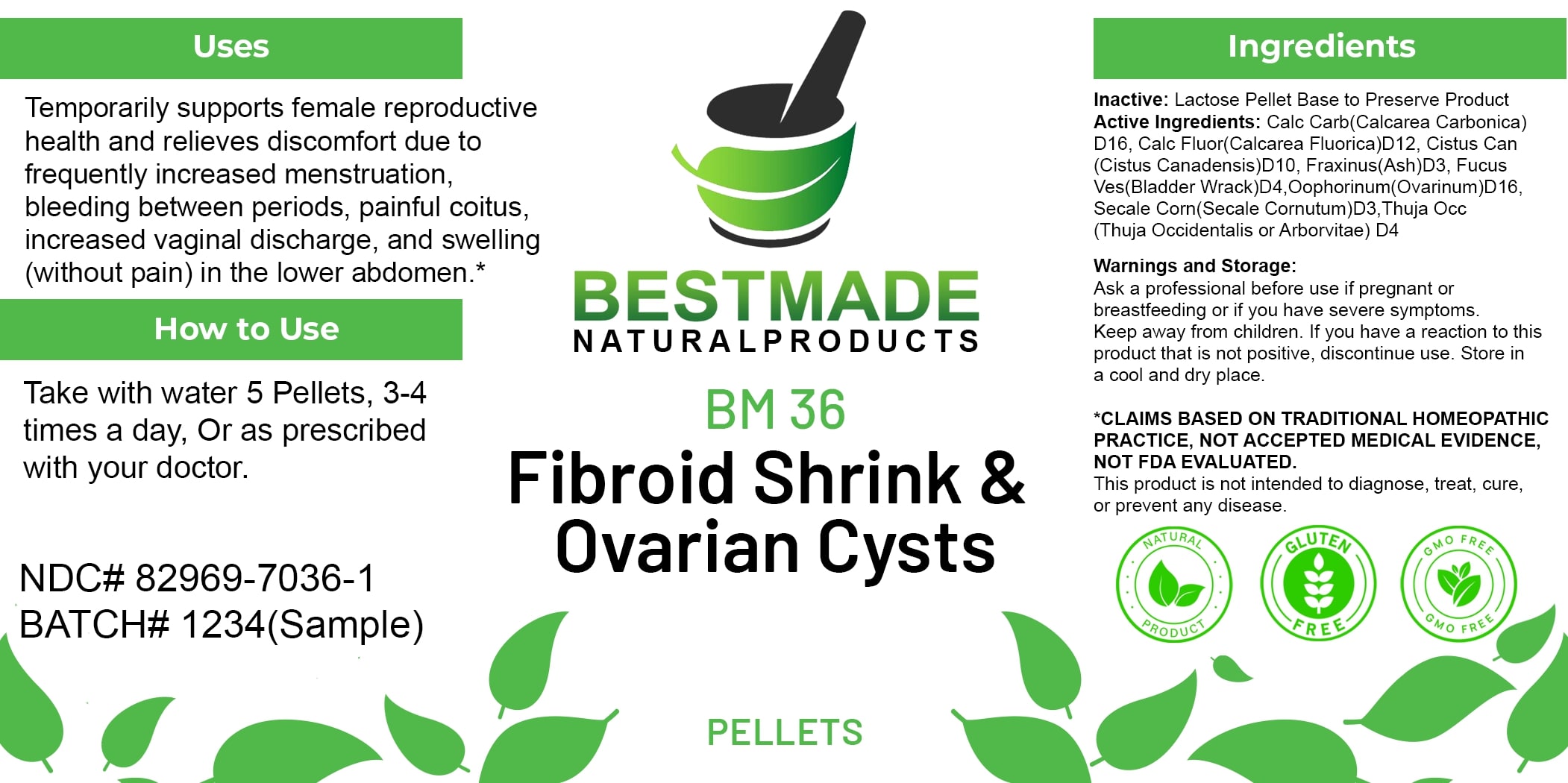 DRUG LABEL: Bestmade Natural Products BM36 Pellets
NDC: 82969-7036 | Form: TABLET, SOLUBLE
Manufacturer: Bestmade Natural Products
Category: homeopathic | Type: HUMAN OTC DRUG LABEL
Date: 20250314

ACTIVE INGREDIENTS: CALCIUM FLUORIDE 30 [hp_C]/30 [hp_C]; CLAVICEPS PURPUREA SCLEROTIUM 30 [hp_C]/30 [hp_C]; CROCANTHEMUM CANADENSE 30 [hp_C]/30 [hp_C]; FRAXINUS AMERICANA BARK 30 [hp_C]/30 [hp_C]; FUCUS VESICULOSUS 30 [hp_C]/30 [hp_C]; THUJA OCCIDENTALIS LEAFY TWIG 30 [hp_C]/30 [hp_C]; OYSTER SHELL CALCIUM CARBONATE, CRUDE 30 [hp_C]/30 [hp_C]; SUS SCROFA OVARY 30 [hp_C]/30 [hp_C]
INACTIVE INGREDIENTS: LACTOSE 30 [hp_C]/30 [hp_C]

BM36 Fibroid Shrink & Ovarian Cysts Pellets

Uses

Temporarily supports female reproductive health and relieves discomfort due to frequently increased menstruation, bleeding between periods, painful coitus, increased vaginal discharge, and swelling (without pain) in the lower abdomen.*

*CLAIMS BASED ON TRADITIONAL HOMEOPATHIC PRACTICE. NOT ACCEPTED MEDICAL EVIDENCE. NOT FDA EVALUATED.

This product is not intended to diagnose, treat, cure, or prevent any disease.

DOSAGE AND ADMINISTRATION

How to Use

Take with water 5 Pellets, 3-4 times a day, Or as prescribed with your doctor.

INACTIVE INGREDIENT

Ingredients

Inactive: Lactose Pellet Base to Preserve Product

ACTIVE INGREDIENT

Active Ingredients: Calc Carb(Calcarea Carbonica) D16, Calc Fluor(Calcarea Fluorica)D12, Cistus Can (Cistus Canadensis)D10, Fraxinus(Ash)D3, Fucus Ves(Bladder Wrack)D4, Oophorinum(Ovarium)D16, Secale Corn(Secale Cornutum)D3, Thuja Occ (Thuja Occidentalis or Arborvitae) D4

Uses

Temporarily supports female reproductive health and relieves discomfort due to frequently increased menstruation, bleeding between periods, painful coitus, increased vaginal discharge, and swelling (without pain) in the lower abdomen.*

*CLAIMS BASED ON TRADITIONAL HOMEOPATHIC PRACTICE. NOT ACCEPTED MEDICAL EVIDENCE. NOT FDA EVALUATED.

This product is not intended to diagnose, treat, cure, or prevent any disease.

KEEP OUT OF REACH OF CHILDREN

Warnings and Storage:

Ask a professional before use if pregnant or breastfeeding or if you have severe symptoms. Keep away from children. If you have a reaction to this product that is not positive, discontinue use. Store in a cool and dry place.

Warnings and Storage:

Ask a professional before use if pregnant or breastfeeding or if you have severe symptoms. Keep away from children. If you have a reaction to this product that is not positive, discontinue use. Store in a cool and dry place.

*CLAIMS BASED ON TRADITIONAL HOMEOPATHIC PRACTICE. NOT ACCEPTED MEDICAL EVIDENCE. NOT FDA EVALUATED.

This product is not intended to diagnose, treat, cure, or prevent any disease.

Entire package label